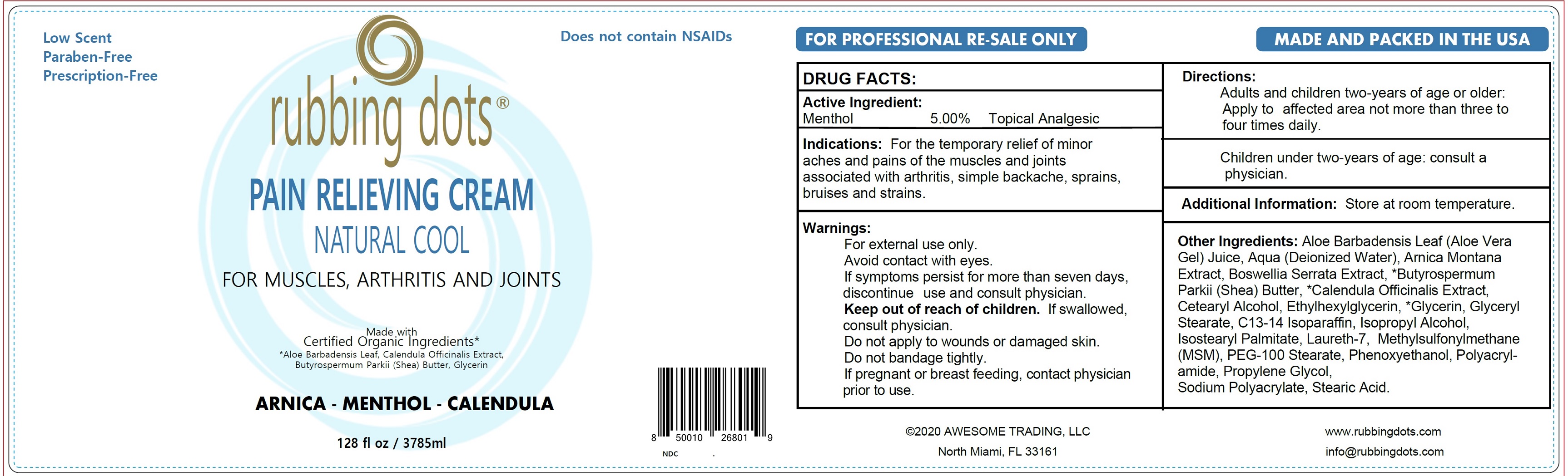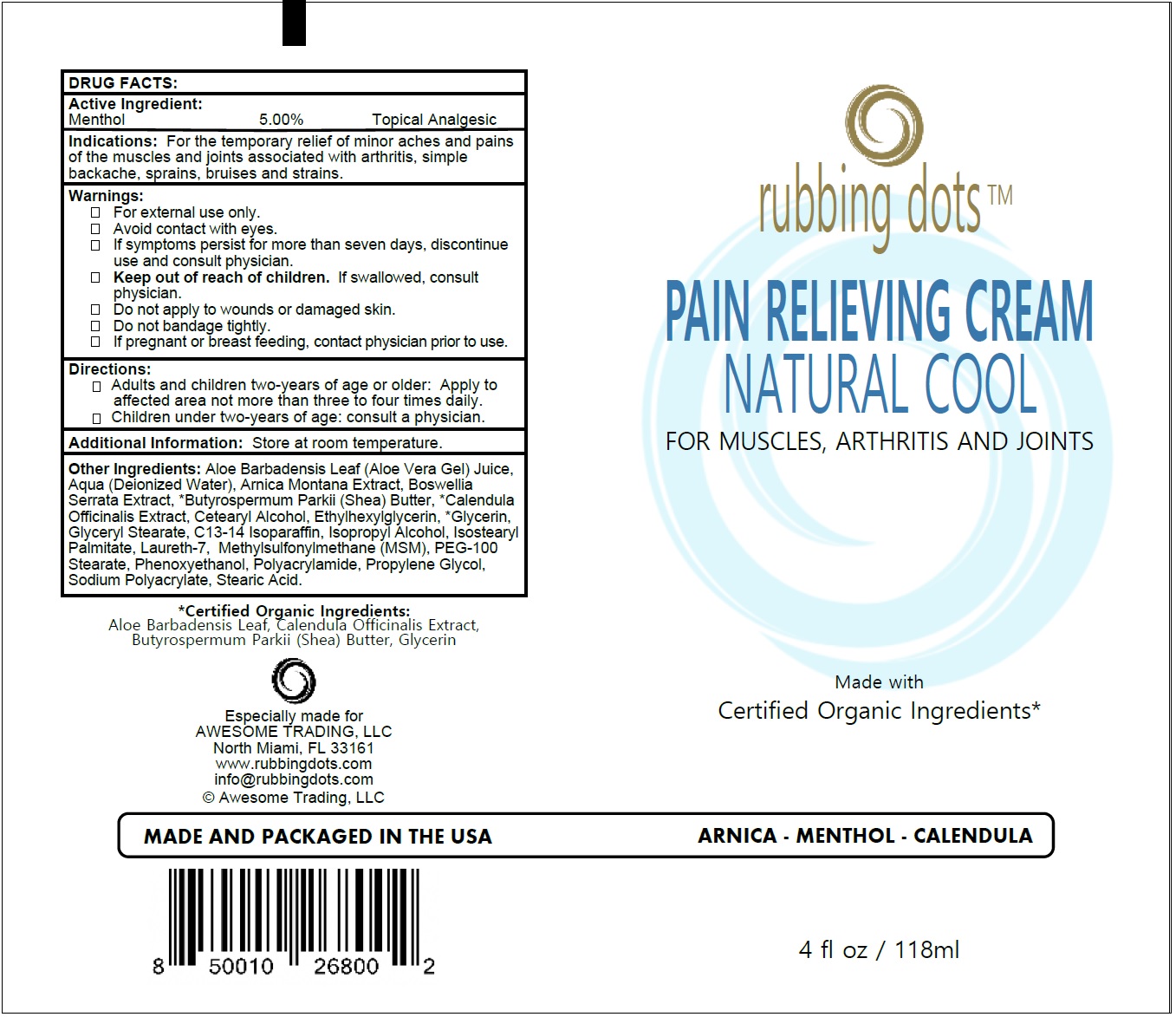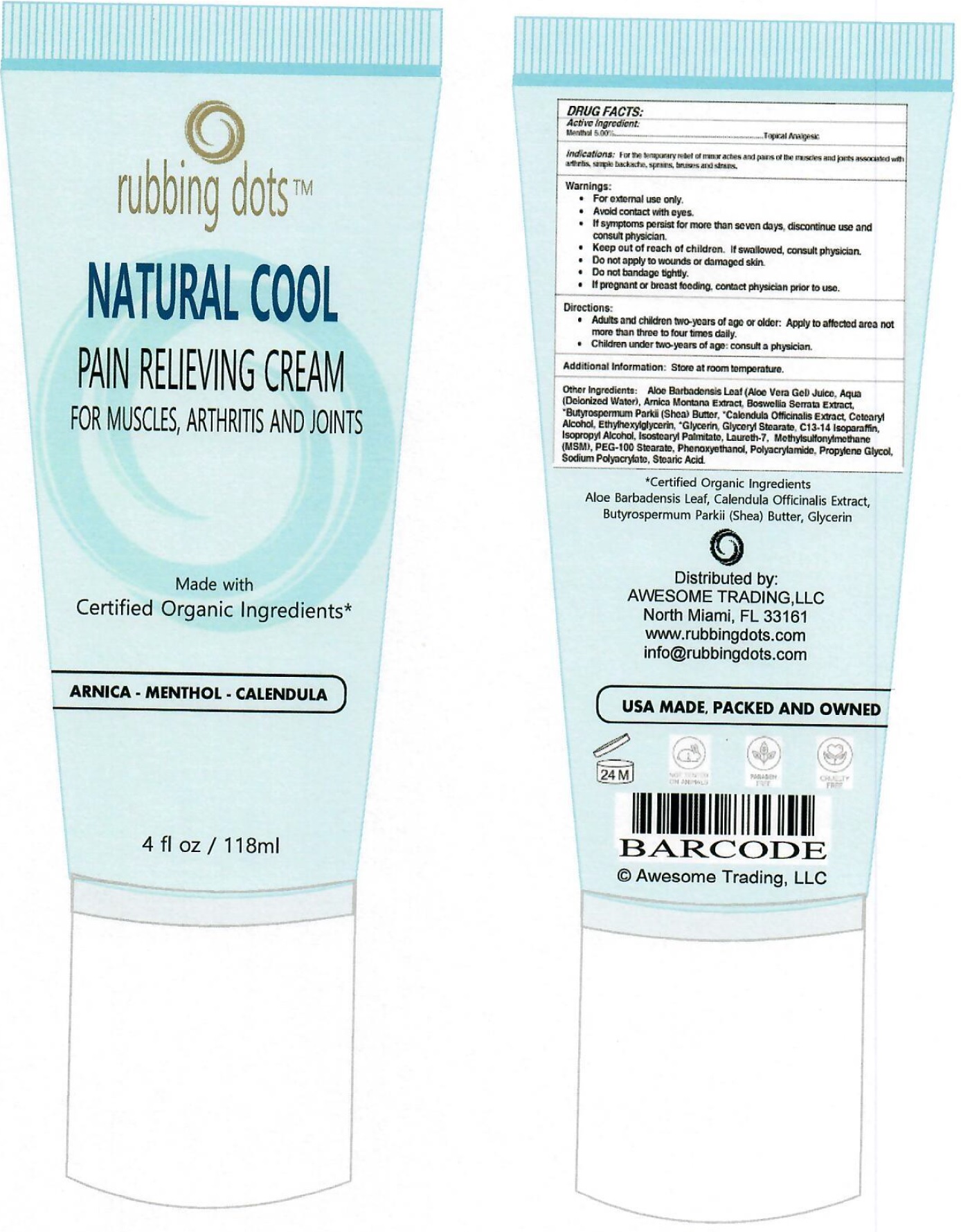 DRUG LABEL: RUBBING DOTS NATURAL COOL PAIN RELIEF
NDC: 73294-005 | Form: CREAM
Manufacturer: Awesome Trading, LLC
Category: otc | Type: HUMAN OTC DRUG LABEL
Date: 20231111

ACTIVE INGREDIENTS: MENTHOL 50 mg/1 mL
INACTIVE INGREDIENTS: ALOE VERA LEAF; WATER; ARNICA MONTANA WHOLE; INDIAN FRANKINCENSE; SHEA BUTTER; CALENDULA OFFICINALIS FLOWER; CETOSTEARYL ALCOHOL; ETHYLHEXYLGLYCERIN; GLYCERIN; GLYCERYL MONOSTEARATE; C13-14 ISOPARAFFIN; ISOPROPYL ALCOHOL; ISOSTEARYL PALMITATE; LAURETH-7; DIMETHYL SULFONE; PEG-100 STEARATE; PHENOXYETHANOL; PROPYLENE GLYCOL; STEARIC ACID

RUBBING DOTS Pain Relieving Cream

Active Ingredient:

Menthol 5.00%

PURPOSE

Topical Analgesic

Indications:

For the temporary relief of minor aches and pains of the muscles and joints associated with arthritis, simple backache, sprains, bruises and strains.

Warnings:

For external use only. Avoid contact with eyes. If symptoms persist for more than seven days, discontinue use and consult physician.

Keep out of reach of children.

If swallowed, consult physician.

Do not apply to wounds or damaged skin.

Do not bandage tightly.

PREGNANCY OR BREAST FEEDING

If pregnant or breast feeding, contact physician prior to use.

Directions:

Adults and children two-years of age or older: Apply to affected area not more than three to four times daily.

Children under two-years of age: consult a physician.

Additional Information:

Store at room temperature.

Other Ingredients:

Aloe Barbadensis Leaf (Aloe Vera Gel) Juice, Aqua (Deionized Water), Arnica Montana Extract, Boswellia Serrata Extract, *Butyrospermum Parkii (Shea) Butter, *Calendula Officinalis Extract, Cetearyl Alcohol, Ethylhexylglycerin, *Glycerin, Glyceryl Stearate, C13-14 Isoparaffin, Isopropyl Alcohol, Isostearyl Palmitate, Laureth-7, Methylsulfonylmethane (MSM), PEG-100 Stearate, Phenoxyethanol, Polyacrylamide, Propylene Glycol, Sodium Polyacrylate, Stearic Acid.